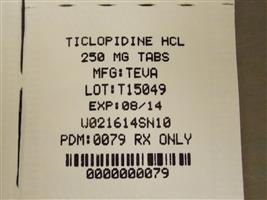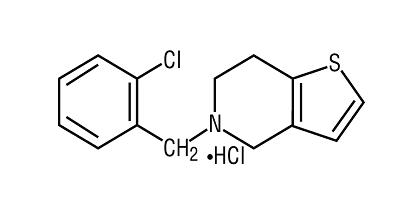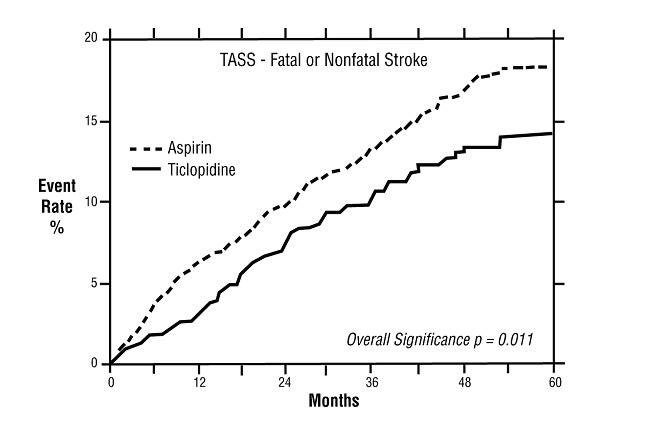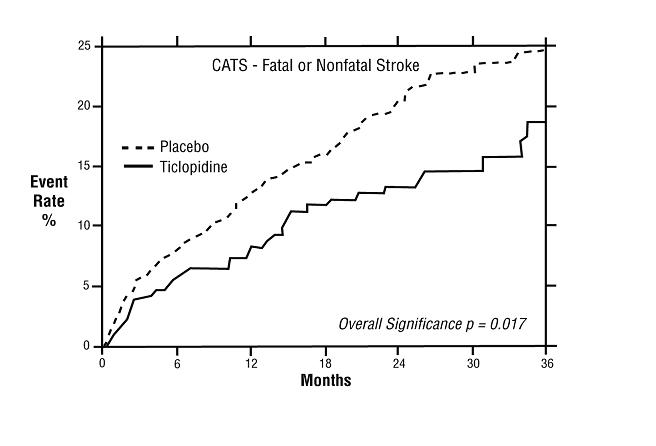 DRUG LABEL: Ticlopidine Hydrochloride
NDC: 68151-0079 | Form: TABLET, FILM COATED
Manufacturer: Carilion Materials Management
Category: prescription | Type: HUMAN PRESCRIPTION DRUG LABEL
Date: 20160806

ACTIVE INGREDIENTS: TICLOPIDINE HYDROCHLORIDE 250 mg/1 1
INACTIVE INGREDIENTS: BUTYLATED HYDROXYANISOLE; STARCH, CORN; HYPROMELLOSES; MAGNESIUM STEARATE; CELLULOSE, MICROCRYSTALLINE; POLYETHYLENE GLYCOLS; POVIDONES; STEARIC ACID; TITANIUM DIOXIDE

TICLOPIDINE HYDROCHLORIDE TABLETS USP 0154 Rx only

WARNING

Ticlopidine can cause life-threatening hematological adverse reactions, including neutropenia/agranulocytosis, thrombotic thrombocytopenic purpura (TTP) and aplastic anemia.

Neutropenia/Agranulocytosis

Among 2048 patients in clinical trials in stroke patients, there were 50 cases (2.4%) of neutropenia (less than 1200 neutrophils/mm), and the neutrophil count was below 450/mm in 17 of these patients (0.8% of the total population).^3^3

TTP

One case of thrombotic thrombocytopenic purpura was reported during clinical trials in stroke patients. Based on postmarketing data, US physicians reported about 100 cases between 1992 and 1997. Based on an estimated patient exposure of 2 million to 4 million, and assuming an event reporting rate of 10% (the true rate is not known), the incidence of ticlopidine-associated TTP may be as high as one case in every 2000 to 4000 patients exposed.

Aplastic Anemia

Aplastic anemia was not seen during clinical trials in stroke patients, but US physicians reported about 50 cases between 1992 and 1998. Based on an estimated patient exposure of 2 million to 4 million, and assuming an event reporting rate of 10% (the true rate is not known), the incidence of ticlopidine-associated aplastic anemia may be as high as one case in every 4000 to 8000 patients exposed.

Monitoring of Clinical and Hematologic Status

Severe hematological adverse reactions may occur within a few days of the start of therapy. The incidence of TTP peaks after about 3 to 4 weeks of therapy and neutropenia peaks at approximately 4 to 6 weeks. The incidence of aplastic anemia peaks after about 4 to 8 weeks of therapy. The incidence of the hematologic adverse reactions declines thereafter. Only a few cases of neutropenia, TTP, or aplastic anemia have arisen after more than 3 months of therapy.

Hematological adverse reactions cannot be reliably predicted by any identified demographic or clinical characteristics. During the first 3 months of treatment, patients receiving ticlopidine must, therefore, be hematologically and clinically monitored for evidence of neutropenia or TTP. If any such evidence is seen, ticlopidine should be immediately discontinued.

The detection and treatment of ticlopidine-associated hematological adverse reactions are further described under WARNINGS.

DESCRIPTION

Ticlopidine hydrochloride is a platelet aggregation inhibitor Chemically it is 5-[(2-chlorophenyl)methyl]-4,5,6,7-tetrahydrothieno [3,2-c] pyridine hydrochloride. The structural formula is: .

C H ClNS •HCl M.W. 300.251414

Ticlopidine hydrochloride is a white crystalline solid. It is freely soluble in water and self-buffers to a pH of 3.6. It also dissolves freely in methanol, is sparingly soluble in methylene chloride and ethanol, slightly soluble in acetone and insoluble in a buffer solution of pH 6.3.

Each tablet, for oral administration, contains 250 mg of ticlopidine hydrochloride. In addition, each tablet also contains the following inactive ingredients: butylated hydroxyanisole, corn starch, hypromellose, magnesium stearate, microcrystalline cellulose, polyethylene glycol, povidone, stearic acid, and titanium dioxide.

CLINICAL PHARMACOLOGY

Mechanism of Action

When taken orally, ticlopidine hydrochloride causes a time- and dose-dependent inhibition of both platelet aggregation and release of platelet granule constituents, as well as a prolongation of bleeding time. The intact drug has no significant activity at the concentrations attained ; and, although analysis of urine and plasma indicates at least 20 metabolites, no metabolite which accounts for the activity of ticlopidine has been isolated. in vitroin vivo

Ticlopidine hydrochloride, after oral ingestion, interferes with platelet membrane function by inhibiting ADP-induced platelet-fibrinogen binding and subsequent platelet-platelet interactions. The effect on platelet function is irreversible for the life of the platelet, as shown both by persistent inhibition of fibrinogen binding after washing platelets and by inhibition of platelet aggregation after resuspension of platelets in buffered medium. ex vivo

Pharmacokinetics and Metabolism

After oral administration of a single 250-mg dose, ticlopidine hydrochloride is rapidly absorbed with peak plasma levels occurring at approximately 2 hours after dosing and is extensively metabolized. Absorption is greater than 80%. Administration after meals results in a 20% increase in the AUC of ticlopidine.

Ticlopidine hydrochloride displays nonlinear pharmacokinetics and clearance decreases markedly on repeated dosing. In older volunteers the apparent half-life of ticlopidine after a single 250-mg dose is about 12.6 hours; with repeat dosing at 250 mg bid, the terminal elimination half-life rises to 4 to 5 days and steady-state levels of ticlopidine hydrochloride in plasma are obtained after approximately 14 to 21 days.

Ticlopidine hydrochloride binds reversibly (98%) to plasma proteins, mainly to serum albumin and lipoproteins. The binding to albumin and lipoproteins is nonsaturable over a wide concentration range. Ticlopidine also binds to alpha-1 acid glycoprotein. At concentrations attained with the recommended dose, only 15% or less ticlopidine in plasma is bound to this protein.

Ticlopidine hydrochloride is metabolized extensively by the liver; only trace amounts of intact drug are detected in the urine. Following an oral dose of radioactive ticlopidine hydrochloride administered in solution, 60% of the radioactivity is recovered in the urine and 23% in the feces. Approximately 1/3 of the dose excreted in the feces is intact ticlopidine hydrochloride, possibly excreted in the bile. Ticlopidine hydrochloride is a minor component in plasma (5%) after a single dose, but at steady-state is the major component (15%). Approximately 40% to 50% of the radioactive metabolites circulating in plasma are covalently bound to plasma proteins, probably by acylation.

Clearance of ticlopidine decreases with age. Steady-state trough values in elderly patients (mean age 70 years) are about twice those in younger volunteer populations.

Hepatically Impaired Patients

The effect of decreased hepatic function on the pharmacokinetics of ticlopidine was studied in 17 patients with advanced cirrhosis. The average plasma concentration of ticlopidine in these subjects was slightly higher than that seen in older subjects in a separate trial (see). CONTRAINDICATIONS

Renally Impaired Patients

Patients with mildly (Ccr 50 to 80 mL/min) or moderately (Ccr 20 to 50 mL/min) impaired renal function were compared to normal subjects (Ccr 80 to 150 mL/min) in a study of the pharmacokinetic and platelet pharmacodynamic effects of ticlopidine (250 mg bid) for 11 days. Concentrations of unchanged ticlopidine were measured after a single 250-mg dose and after the final 250-mg dose on Day 11.

AUC values of ticlopidine increased by 28% and 60% in mild and moderately impaired patients, respectively, and plasma clearance decreased by 37% and 52%, respectively, but there were no statistically significant differences in ADP-induced platelet aggregation. In this small study (26 patients), bleeding times showed significant prolongation only in the moderately impaired patients.

Pharmacodynamics

In healthy volunteers over the age of 50, substantial inhibition (over 50%) of ADP-induced platelet aggregation is detected within 4 days after administration of ticlopidine hydrochloride 250 mg bid, and maximum platelet aggregation inhibition (60% to 70%) is achieved after 8 to 11 days. Lower doses cause less, and more delayed, platelet aggregation inhibition, while doses above 250 mg bid give little additional effect on platelet aggregation but an increased rate of adverse effects. The dose of 250 mg bid is the only dose that has been evaluated in controlled clinical trials.

After discontinuation of ticlopidine hydrochloride, bleeding time and other platelet function tests return to normal within 2 weeks, in the majority of patients.

At the recommended therapeutic dose (250 mg bid), ticlopidine hydrochloride has no known significant pharmacological actions in man other than inhibition of platelet function and prolongation of the bleeding time.

CLINICAL TRIALS

Stroke Patients

The effect of ticlopidine on the risk of stroke and cardiovascular events was studied in two multicenter, randomized, double-blind trials.

1. Study in Patients Experiencing Stroke Precursors

In a trial comparing ticlopidine and aspirin (The Ticlopidine Aspirin Stroke Study or TASS), 3069 patients (1987 men, 1082 women) who had experienced such stroke precursors as transient ischemic attack (TIA), transient monocular blindness (amaurosis fugax), reversible ischemic neurological deficit or minor stroke, were randomized to ticlopidine 250 mg bid or aspirin 650 mg bid. The study was designed to follow patients for at least 2 years and up to 5 years.

Over the duration of the study, ticlopidine significantly reduced the risk of fatal and nonfatal stroke by 24% (p =.011) from 18.1 to 13.8 per 100 patients followed for 5 years, compared to aspirin. During the first year, when the risk of stroke is greatest, the reduction in risk of stroke (fatal and nonfatal) compared to aspirin was 48%; the reduction was similar in men and women.

2. Study in Patients Who Had a Completed Atherothrombotic Stroke

In a trial comparing ticlopidine with placebo (The Canadian American Ticlopidine Study or CATS) 1073 patients who had experienced a previous atherothrombotic stroke were treated with ticlopidine 250 mg bid or placebo for up to 3 years.

Ticlopidine significantly reduced the overall risk of stroke by 24% (p=.017) from 24.6 to 18.6 per 100 patients followed for 3 years, compared to placebo. During the first year the reduction in risk of fatal and nonfatal stroke over placebo was 33%.

Stent Patients

The ability of ticlopidine to reduce the rate of thrombotic events after the placement of coronary artery stents has been studied in five randomized trials, one of substantial size (Stent Anticoagulation Restenosis Study or STARS) described below, and four smaller studies. In these trials, ticlopidine 250 mg bid with ASA (dose range from 100 mg bid to 325 mg qd) was compared to aspirin alone or to anticoagulant therapy plus aspirin. The trials enrolled patients undergoing both planned (elective) and unplanned coronary stent placement. The types of stents used, the use of intravascular ultrasound, and the use of high-pressure stent deployment varied among the trials, although all patients in STARS received a Palmaz-Schatz stent. The primary efficacy endpoints of the trials were similar, and included death, myocardial infarction and the need for repeat coronary angioplasty or CABG. All trials followed patients for at least 30 days.

In STARS, patients were randomized to receive one of three regimens for 4 weeks: aspirin alone, aspirin plus coumadin, or aspirin plus ticlopidine. Therapy was initiated following successful coronary stent placement. The primary endpoint was the incidence of stent thrombosis, defined as death, Q-Wave MI, or angiographic thrombus within the stented vessel demonstrated at the time of documented ischemia requiring emergent revascularization. The incidence rates for the primary endpoint and its components at 30 days are shown in the table below.

STARS | Ticlopidine + Aspirin N=546 | Aspirin N=557 | Coumadin + Aspirin N=550 | Odds Ratio (95% C.I.) [Comparison of ticlopidine plus aspirin to aspirin alone.] | p-Value
Primary Endpoint | 3 (0.5%) | 20 (3.6%) | 15 (2.7%) | 0.15 (0.03, 0.51) | <0.001
Deaths | 0 (0%) | 1 (0.2%) | 0 (0%) | - | -
Q-Wave MI (Recurrent and Procedure Related) | 1 (0.2%) | 12 (2.2%) | 8 (1.5%) | 0.08 (0.002, 0.57) | 0.004
Angiographically Evident Thrombosis | 3 (0.5%) | 16 (2.9%) | 15 (2.7%) | 0.19 (0.03, 0.66) | 0.005

The use of ticlopidine plus aspirin did not affect the rate of non-Q-wave MIs when compared with aspirin alone or aspirin plus anticoagulants in STARS.

The use of ticlopidine plus aspirin was associated with a lower rate of recurrent cardiovascular events when compared with aspirin alone or aspirin plus anticoagulants in the other four randomized trials.

The rate of serious bleeding complications and neutropenia in STARS are shown in the table below. There were no cases of thrombotic thrombocytopenic purpura (TTP) or aplastic anemia reported in 1346 patients who received ticlopidine plus aspirin in the five randomized trials.

STARS | Ticlopidine + Aspirin N=546 | Aspirin N=557 | Coumadin + Aspirin N=550
Hemorrhagic Complications | 30 (5.5%) | 10 (1.8%) | 34 (6.2%)
Cerebrovascular Accident | 0 (0%) | 2 (0.4%) | 1 (0.2%)
Neutropenia (≤ 1200/mm ^3) | 3 (0.5%) | 0 (0%) | 1 (0.2%)

INDICATIONS AND USAGE

Ticlopidine Hydrochloride Tablets USP are indicated:

- to reduce the risk of thrombotic stroke (fatal or nonfatal) in patients who have experienced stroke precursors, and in patients who have had a completed thrombotic stroke. Because ticlopidine is associated with a risk of life-threatening blood dyscrasias including thrombotic thrombocytopenic purpura (TTP), neutropenia/agranulocytosis and aplastic anemia (see and), ticlopidine should be reserved for patients who are intolerant or allergic to aspirin therapy or who have failed aspirin therapy. BOXED WARNINGWARNINGS
- as adjunctive therapy with aspirin to reduce the incidence of subacute stent thrombosis in patients undergoing successful coronary stent implantation (see). CLINICAL TRIALS

CONTRAINDICATIONS

The use of ticlopidine is contraindicated in the following conditions:

- Hypersensitivity to the drug
- Presence of hematopoietic disorders such as neutropenia and thrombocytopenia or a past history of either TTP or aplastic anemia
- Presence of a hemostatic disorder or active pathological bleeding (such as bleeding peptic ulcer or intracranial bleeding)
- Patients with severe liver impairment

WARNINGS

Hematological Adverse Reactions

Neutropenia

Neutropenia may occur suddenly. Bone-marrow examination typically shows a reduction in white blood cell precursors. After withdrawal of ticlopidine, the neutrophil count usually rises to >1200/mm within 1 to 3 weeks.^3

Thrombocytopenia

Rarely, thrombocytopenia may occur in isolation or together with neutropenia.

Thrombotic Thrombocytopenic Purpura (TTP)

TTP is characterized by thrombocytopenia, microangiopathic hemolytic anemia (schistocytes [fragmented RBCs] seen on peripheral smear), neurological findings, renal dysfunction, and fever. The signs and symptoms can occur in any order, in particular, clinical symptoms may precede laboratory findings by hours or days. With treatment (often including plasmapheresis), 70% to 80% of patients will survive with minimal or no sequelae. Because platelet transfusions may accelerate thrombosis in patients with TTP on ticlopidine, they should, if possible, be avoided. prompt

Aplastic Anemia

Aplastic anemia is characterized by anemia, thrombocytopenia and neutropenia together with a bone marrow examination that shows decreases in the precursor cells for red blood cells, white blood cells, and platelets. Patients may present with signs or symptoms suggestive of infection, in association with low white blood cell and platelet counts. treatment, which may include the use of drugs to stimulate the bone marrow, can minimize the mortality associated with aplastic anemia. Prompt

Monitoring for Hematologic Adverse Reactions

Starting just before initiating treatment and continuing through the third month of therapy, patients receiving ticlopidine must be monitored every 2 weeks. Because of ticlopidine’s long plasma half-life, patients who discontinue ticlopidine during this 3-month period should continue to be monitored for 2 weeks after discontinuation. More frequent monitoring, and monitoring after the first 3 months of therapy, is necessary only in patients with clinical signs (eg, signs or symptoms suggestive of infection) or laboratory signs (eg, neutrophil count less than 70% of the baseline count, decrease in hematocrit or platelet count) that suggest incipient hematological adverse reactions.

Clinically, fever might suggest neutropenia, TTP, or aplastic anemia; TTP might also be suggested by weakness, pallor, petechiae or purpura, dark urine (due to blood, bile pigments, or hemoglobin) or jaundice, or neurological changes. Patients should be told to discontinue ticlopidine and to contact the physician immediately upon the occurrence of any of these findings.

Laboratory monitoring should include a complete blood count, with special attention to the absolute neutrophil count (WBC x % neutrophils), platelet count, and the appearance of the peripheral smear. Ticlopidine is occasionally associated with thrombocytopenia unrelated to TTP or aplastic anemia. Any acute, unexplained reduction in or platelet count should prompt further investigation for a diagnosis of TTP, and the appearance of (fragmented RBCs) on the smear should be treated as presumptive evidence of TTP. A simultaneous decrease in platelet count and WBC count should prompt further investigation for a diagnosis of aplastic anemia. If there are laboratory signs of TTP or aplastic anemia, or if the neutrophil count is confirmed to be <1200/mm , then ticlopidine should be discontinued immediately. hemoglobinschistocytes^3

Other Hematological Effects

Rare cases of agranulocytosis, pancytopenia, or leukemia have been reported in postmarketing experience, some of which have been fatal. All forms of hematological adverse reactions are potentially fatal.

Cholesterol Elevation

Ticlopidine therapy causes increased serum cholesterol and triglycerides. Serum total cholesterol levels are increased 8% to 10% within 1 month of therapy and persist at that level. The ratios of the lipoprotein subfractions are unchanged.

Anticoagulant Drugs

The tolerance and long-term safety of coadministration of ticlopidine with heparin, oral anticoagulants or fibrinolytic agents have not been established. In trials for cardiac stenting, patients received heparin and ticlopidine concomitantly for approximately 12 hours. If a patient is switched from an anticoagulant or fibrinolytic drug to ticlopidine, the former drug should be discontinued prior to ticlopidine administration.

PRECAUTIONS

General

Ticlopidine should be used with caution in patients who may be at risk of increased bleeding from trauma, surgery or pathological conditions. If it is desired to eliminate the antiplatelet effects of ticlopidine prior to elective surgery, the drug should be discontinued 10 to 14 days prior to surgery. Several controlled clinical studies have found increased surgical blood loss in patients undergoing surgery during treatment with ticlopidine. In TASS and CATS it was recommended that patients have ticlopidine discontinued prior to elective surgery. Several hundred patients underwent surgery during the trials, and no excessive surgical bleeding was reported.

Prolonged bleeding time is normalized within 2 hours after administration of 20 mg methylprednisolone IV. Platelet transfusions may also be used to reverse the effect of ticlopidine on bleeding. Because platelet transfusions may accelerate thrombosis in patients with TTP on ticlopidine, they should, if possible, be avoided.

GI Bleeding

Ticlopidine prolongs template bleeding time. The drug should be used with caution in patients who have lesions with a propensity to bleed (such as ulcers). Drugs that might induce such lesions should be used with caution in patients on ticlopidine (see). CONTRAINDICATIONS

Use in Hepatically Impaired Patients

Since ticlopidine is metabolized by the liver, dosing of ticlopidine or other drugs metabolized in the liver may require adjustment upon starting or stopping concomitant therapy. Because of limited experience in patients with severe hepatic disease, who may have bleeding diatheses, the use of ticlopidine is not recommended in this population (see and). CLINICAL PHARMACOLOGYCONTRAINDICATIONS

Use in Renally Impaired Patients

There is limited experience in patients with renal impairment. Decreased plasma clearance, increased AUC values and prolonged bleeding times can occur in renally impaired patients. In controlled clinical trials no unexpected problems have been encountered in patients having mild renal impairment, and there is no experience with dosage adjustment in patients with greater degrees of renal impairment. Nevertheless, for renally impaired patients, it may be necessary to reduce the dosage of ticlopidine or discontinue it altogether if hemorrhagic or hematopoietic problems are encountered (see). CLINICAL PHARMACOLOGY

Information for the Patient (see Patient Leaflet)

Patients should be told that a decrease in the number of white blood cells (neutropenia) or platelets (thrombocytopenia) can occur with ticlopidine, especially during the first 3 months of treatment and that neutropenia, if it is severe, can result in an increased risk of infection. They should be told it is critically important to obtain the scheduled blood tests to detect neutropenia or thrombocytopenia. Patients should also be reminded to contact their physicians if they experience any indication of infection such as fever, chills, or sore throat, any of which might be a consequence of neutropenia. Thrombocytopenia may be part of a syndrome called TTP. Symptoms and signs of TTP, such as fever, weakness, difficulty speaking, seizures, yellowing of skin or eyes, dark or bloody urine, pallor or petechiae (pinpoint hemorrhagic spots on the skin), should be reported immediately.

All patients should be told that it may take them longer than usual to stop bleeding when they take ticlopidine and that they should report any unusual bleeding to their physician. Patients should tell physicians and dentists that they are taking ticlopidine before any surgery is scheduled and before any new drug is prescribed.

Patients should be told to promptly report side effects of ticlopidine such as severe or persistent diarrhea, skin rashes or subcutaneous bleeding or any signs of cholestasis, such as yellow skin or sclera, dark urine, or light-colored stools.

Patients should be told to take ticlopidine with food or just after eating in order to minimize gastrointestinal discomfort.

Laboratory Tests

Liver Function

Ticlopidine therapy has been associated with elevations of alkaline phosphatase, bilirubin, and transaminases, which generally occurred within 1 to 4 months of therapy initiation. In controlled clinical trials in stroke patients, the incidence of elevated alkaline phosphatase (greater than two times upper limit of normal) was 7.6% in ticlopidine patients, 6% in placebo patients and 2.5% in aspirin patients. The incidence of elevated AST (SGOT) (greater than two times upper limit of normal) was 3.1% in ticlopidine patients, 4% in placebo patients and 2.1% in aspirin patients. No progressive increases were observed in closely monitored clinical trials (eg, no transaminase greater than 10 times the upper limit of normal was seen), but most patients with these abnormalities had therapy discontinued. Occasionally patients had developed minor elevations in bilirubin.

Postmarketing experience includes rare individuals with elevations in their transaminases and bilirubin to >10X above the upper limits of normal. Based on postmarketing and clinical trial experience, liver function testing, including ALT, AST, and GGT, should be considered whenever liver dysfunction is suspected, particularly during the first 4 months of treatment.

Drug Interactions

Therapeutic doses of ticlopidine caused a 30% increase in the plasma half-life of antipyrine and may cause analogous effects on similarly metabolized drugs. Therefore, the dose of drugs metabolized by hepatic microsomal enzymes with low therapeutic ratios or being given to patients with hepatic impairment may require adjustment to maintain optimal therapeutic blood levels when starting or stopping concomitant therapy with ticlopidine. Studies of specific drug interactions yielded the following results:

Aspirin and other NSAIDs

Ticlopidine potentiates the effect of aspirin or other NSAIDs on platelet aggregation. The safety of concomitant use of ticlopidine and NSAIDs has not been established. The safety of concomitant use of ticlopidine and aspirin beyond 30 days has not been established (see :). Aspirin did not modify the ticlopidine-mediated inhibition of ADP-induced platelet aggregation, but ticlopidine potentiated the effect of aspirin on collagen-induced platelet aggregation. Caution should be exercised in patients who have lesions with a propensity to bleed, such as ulcers. Long-term concomitant use of aspirin and ticlopidine is not recommended (see :). CLINICAL TRIALSStent Patients PRECAUTIONSGI Bleeding

Antacids

Administration of ticlopidine after antacids resulted in an 18% decrease in plasma levels of ticlopidine.

Cimetidine

Chronic administration of cimetidine reduced the clearance of a single dose of ticlopidine by 50%.

Digoxin

Coadministration of ticlopidine with digoxin resulted in a slight decrease (approximately 15%) in digoxin plasma levels. Little or no change in therapeutic efficacy of digoxin would be expected.

Theophylline

In normal volunteers, concomitant administration of ticlopidine resulted in a significant increase in the theophylline elimination half-life from 8.6 to 12.2 hours and a comparable reduction in total plasma clearance of theophylline.

Phenobarbital

In 6 normal volunteers, the inhibitory effects of ticlopidine on platelet aggregation were not altered by chronic administration of phenobarbital.

Phenytoin

studies demonstrated that ticlopidine does not alter the plasma protein binding of phenytoin. However, the protein binding interactions of ticlopidine and its metabolites have not been studied . Several cases of elevated phenytoin plasma levels with associated somnolence and lethargy have been reported following coadministration with ticlopidine. Caution should be exercised in coadministering this drug with ticlopidine, and it may be useful to remeasure phenytoin blood concentrations. In vitroin vivo

Propranolol

studies demonstrated that ticlopidine does not alter the plasma protein binding of propranolol. However, the protein binding interactions of ticlopidine and its metabolites have not been studied . Caution should be exercised in coadministering this drug with ticlopidine. In vitroin vivo

Other Concomitant Therapy

Although specific interaction studies were not performed, in clinical studies ticlopidine was used concomitantly with beta blockers, calcium channel blockers and diuretics without evidence of clinically significant adverse interactions (see). PRECAUTIONS

Food Interaction

The oral bioavailability of ticlopidine is increased by 20% when taken after a meal. Administration of ticlopidine with food is recommended to maximize gastrointestinal tolerance. In controlled trials in stroke patients, ticlopidine was taken with meals.

Carcinogenesis, Mutagenesis, Impairment of Fertility

In a 2-year oral carcinogenicity study in rats, ticlopidine at daily doses of up to 100 mg/kg (610 mg/m) was not tumorigenic. For a 70-kg person (1.73 m body surface area) the dose represents 14 times the recommended clinical dose on a mg/kg basis and two times the clinical dose on body surface area basis. In a 78-week oral carcinogenicity study in mice, ticlopidine at daily doses up to 275 mg/kg (1180 mg/m) was not tumorigenic. The dose represents 40 times the recommended clinical dose on a mg/kg basis and four times the clinical dose on body surface area basis.^2^2^2

Ticlopidine was not mutagenic in the Ames test, the rat hepatocyte DNA-repair assay, or the Chinese-hamster fibroblast chromosomal aberration test; or in the mouse spermatozoid morphology test, the Chinese-hamster micronucleus test, or the Chinese-hamster bone-marrow-cell sister-chromatid exchange test. Ticlopidine was found to have no effect on fertility of male and female rats at oral doses up to 400 mg/kg/day. in vitroin vivo

Pregnancy

Teratogenic Effects

Pregnancy category B

Teratology studies have been conducted in mice (doses up to 200 mg/kg/day), rats (doses up to 400 mg/kg/day) and rabbits (doses up to 200 mg/kg/day). Doses of 400 mg/kg in rats, 200 mg/kg/day in mice and 100 mg/kg in rabbits produced maternal toxicity, as well as fetal toxicity, but there was no evidence of a teratogenic potential of ticlopidine. There are, however, no adequate and well-controlled studies in pregnant women. Because animal reproduction studies are not always predictive of a human response, this drug should be used during pregnancy only if clearly needed.

Nursing Mothers

Studies in rats have shown ticlopidine is excreted in the milk. It is not known whether this drug is excreted in human milk. Because many drugs are excreted in human milk and because of the potential for serious adverse reactions in nursing infants from ticlopidine, a decision should be made whether to discontinue nursing or to discontinue the drug, taking into account the importance of the drug to the mother.

Pediatric Use

Safety and effectiveness in pediatric patients have not been established.

Geriatric Use

Clearance of ticlopidine is somewhat lower in elderly patients and trough levels are increased. The major clinical trials with ticlopidine in stroke patients were conducted in an elderly population with an average age of 64 years. Of the total number of patients in the therapeutic trials, 45% of patients were over 65 years old and 12% were over 75 years old. No overall differences in effectiveness or safety were observed between these patients and younger patients, and other reported clinical experience has not identified differences in responses between the elderly and younger patients, but greater sensitivity of some older individuals cannot be ruled out.

ADVERSE REACTIONS

Adverse reactions in stroke patients were relatively frequent with over 50% of patients reporting at least one. Most (30% to 40%) involved the gastrointestinal tract. Most adverse effects are mild, but 21% of patients discontinued therapy because of an adverse event, principally diarrhea, rash, nausea, vomiting, GI pain and neutropenia. Most adverse effects occur early in the course of treatment, but a new onset of adverse effects can occur after several months.

The incidence rates of adverse events listed in the following table were derived from multicenter, controlled clinical trials in stroke patients described above comparing ticlopidine, placebo and aspirin over study periods of up to 5.8 years. Adverse events considered by the investigator to be probably drug-related that occurred in at least 1% of patients treated with ticlopidine are shown in the following table:

Percent of Patients with Adverse Events in Controlled Studies (TASS and CATS)
Event | Ticlopidine (n = 2048) Incidence | Aspirin (n = 1527) Incidence | Placebo (n = 536) Incidence
Any Events | 60.0 (20.9) | 53.2 (14.5) | 34.3 (6.1)
Diarrhea | 12.5 (6.3) | 5.2 (1.8) | 4.5 (1.7)
Nausea | 7.0 (2.6) | 6.2 (1.9) | 1.7 (0.9)
Dyspepsia | 7.0 (1.1) | 9.0 (2.0) | 0.9 (0.2)
Rash | 5.1 (3.4) | 1.5 (0.8) | 0.6 (0.9)
GI Pain | 3.7 (1.9) | 5.6 (2.7) | 1.3 (0.4)
Neutropenia | 2.4 (1.3) | 0.8 (0.1) | 1.1 (0.4)
Purpura | 2.2 (0.2) | 1.6 (0.1) | 0.0 (0.0)
Vomiting | 1.9 (1.4) | 1.4 (0.9) | 0.9 (0.4)
Flatulence | 1.5 (0.1) | 1.4 (0.3) | 0.0 (0.0)
Pruritus | 1.3 (0.8) | 0.3 (0.1) | 0.0 (0.0)
Dizziness | 1.1 (0.4) | 0.5 (0.4) | 0.0 (0.0)
Anorexia | 1.0 (0.4) | 0.5 (0.3) | 0.0 (0.0)
Abnormal Liver Function Test | 1.0 (0.7) | 0.3 (0.3) | 0.0 (0.0)

Incidence of discontinuation, regardless of relationship to therapy, is shown in parentheses.

Hematological

Neutropenia/thrombocytopenia, TTP, aplastic anemia (see and), leukemia, agranulocytosis, eosinophilia, pancytopenia, thrombocytosis and bone-marrow depression have been reported. BOXED WARNINGWARNINGS

Gastrointestinal

Ticlopidine therapy has been associated with a variety of gastrointestinal complaints including diarrhea and nausea. The majority of cases are mild, but about 13% of patients discontinued therapy because of these. They usually occur within 3 months of initiation of therapy and typically are resolved within 1 to 2 weeks without discontinuation of therapy. If the effect is severe or persistent, therapy should be discontinued. In some cases of severe or bloody diarrhea, colitis was later diagnosed.

Hemorrhagic

Ticlopidine has been associated with increased bleeding, spontaneous posttraumatic bleeding and perioperative bleeding including, but not limited to, gastrointestinal bleeding. It has also been associated with a number of bleeding complications such as ecchymosis, epistaxis, hematuria and conjunctival hemorrhage.

Intracerebral bleeding was rare in clinical trials in stroke patients with ticlopidine, with an incidence no greater than that seen with comparator agents (ticlopidine 0.5%, aspirin 0.6%, placebo 0.75%). It has also been reported postmarketing.

Rash

Ticlopidine has been associated with a maculopapular or urticarial rash (often with pruritus). Rash usually occurs within 3 months of initiation of therapy with a mean onset time of 11 days. If drug is discontinued, recovery occurs within several days. Many rashes do not recur on drug rechallenge. There have been rare reports of severe rashes, including Stevens-Johnson syndrome, erythema multiforme and exfoliative dermatitis.

Less Frequent Adverse Reactions (Probably Related)

Clinical adverse experiences occurring in 0.5% to 1.0% of stroke patients in controlled trials include:

Digestive System: GI fullness

Skin and Appendages: urticaria

Nervous System: headache

Body as a Whole: asthenia, pain

Hemostatic System: epistaxis

Special Senses: tinnitus

In addition, rarer, relatively serious and potentially fatal events associated with the use of ticlopidine have also been reported from postmarketing experience: Hemolytic anemia with reticulocytosis, immune thrombocytopenia, hepatitis, hepatocellular jaundice, cholestatic jaundice, hepatic necrosis, hepatic failure, peptic ulcer, renal failure, nephrotic syndrome, hyponatremia, vasculitis, sepsis, allergic reactions (including angioedema, allergic pneumonitis, and anaphylaxis), systemic lupus (positive ANA), peripheral neuropathy, serum sickness, arthropathy and myositis.

OVERDOSAGE

One case of deliberate overdosage with ticlopidine has been reported by a foreign postmarketing surveillance program. A 38-year-old male took a single 6000-mg dose of ticlopidine hydrochloride (equivalent to 24 standard 250-mg tablets). The only abnormalities reported were increased bleeding time and increased SGPT. No special therapy was instituted and the patient recovered without sequelae.

Single oral doses of ticlopidine at 1600 mg/kg and 500 mg/kg were lethal to rats and mice, respectively. Symptoms of acute toxicity were GI hemorrhage, convulsions, hypothermia, dyspnea, loss of equilibrium and abnormal gait.

DOSAGE AND ADMINISTRATION

Stroke

The recommended dose of ticlopidine hydrochloride is 250 mg bid taken with food. Other doses have not been studied in controlled trials for these indications.

Coronary Artery Stenting

The recommended dose of ticlopidine hydrochloride is 250 mg bid taken with food together with antiplatelet doses of aspirin for up to 30 days of therapy following successful stent implantation.

HOW SUPPLIED

NDC:68151-0079-0 in a BOTTLE of 1 TABLET, FILM COATEDS

IMPORTANT INFORMATION ABOUT TICLOPIDINE HYDROCHLORIDE TABLETS USP

The information in this leaflet is intended to help you use ticlopidine hydrochloride tablets safely. Please read the leaflet carefully. Although it does not contain all the detailed medical information that is provided to your doctor, it provides facts about ticlopidine hydrochloride tablets that are important for you to know. If you still have questions after reading this leaflet or if you have questions at any time during your treatment with ticlopidine hydrochloride tablets, check with your doctor.

Why Ticlopidine Hydrochloride Tablets Were Prescribed by Your Doctor:

Stroke Patients: Ticlopidine hydrochloride tablets are recommended to help reduce your risk of having a stroke, but only for patients who have had a stroke or early stroke warning symptoms while on aspirin, or for those who have these symptoms but are intolerant or allergic to aspirin.

Stent Patients: Ticlopidine hydrochloride tablets are recommended with aspirin for up to 30 days in patients who have had a stent implanted in their coronary arteries to reduce the risk of blood clots forming inside the stent.

Ticlopidine hydrochloride tablets are not prescribed for those who can take aspirin to reduce the risk of stroke because ticlopidine hydrochloride tablets can cause life-threatening blood problems. Special Warning for Users of Ticlopidine Hydrochloride Tablets/Necessary Blood Tests: Getting your blood tests done and reporting symptoms to your doctor as soon as possible can avoid serious complications.

The white cells of the blood that fight infection may drop to dangerous levels (a condition called neutropenia). This occurs in about 2.4% (1 in 40) of people on ticlopidine. You should be on the lookout for signs of infection such as fever, chills or sore throat. If this problem is caught early, it can almost always be reversed, but if undetected it can be fatal.

Another problem that has occurred in some patients taking ticlopidine is a decrease in cells called platelets (a condition called thrombocytopenia). This may occur as part of a syndrome that includes injury to red blood cells, causing anemia, kidney abnormalities, neurologic changes and fever. This condition is called TTP and can be fatal.

Things you should watch for as possible early signs of TTP are yellow skin or eye color, pinpoint dots (rash) on the skin, pale color, fever, weakness on a side of the body, or dark urine. If any of these occur, contact your doctor immediately.

Both complications occur most frequently in the first 90 days after ticlopidine hydrochloride tablets are started. To make sure you don’t develop either of these problems, If detected, neutropenia and thrombocytopenia can almost always be reversed. It is that you keep your appointments for the blood tests and that you call your doctor immediately if you have any indication that you may have TTP or neutropenia. If you stop taking ticlopidine hydrochloride tablets for any reason within the first 3 months, you will still need to have your blood tested for an additional 2 weeks after you have stopped taking ticlopidine hydrochloride tablets. your doctor will arrange for you to have your blood tested before you start taking ticlopidine hydrochloride tablets and then every 2 weeks for the first 3 months you are on ticlopidine hydrochloride tablets. essential

Rarely, decreases in the white blood cells, red blood cells and platelets can occur together. This condition is called aplastic anemia and can be fatal.

Things you should watch for as possible early signs of aplastic anemia are feeling of excessive weakness and tiredness, paleness, bruising, and bleeding from areas such as your nose or gums. You may also develop signs of infection such as fever. If any of these occur, contact your doctor immediately.

A few people may develop jaundice while being treated with ticlopidine hydrochloride tablets. The signs of jaundice are yellowing of the skin or the whites of the eyes or consistent darkening of the urine or lightening in the color of the stools. These symptoms should be reported to your physician promptly. Other Warnings and Precautions:

If any of the symptoms described above for neutropenia, TTP, aplastic anemia or jaundice occur, contact your doctor immediately.

Ticlopidine hydrochloride tablets should be used only as directed by your doctor. Do not give ticlopidine hydrochloride tablets to anyone else. Keep ticlopidine hydrochloride tablets out of reach of children!

Some people may have such side effects as diarrhea, skin rash, stomach or intestinal discomfort. If any of these problems are persistent, or if you are concerned about them, bring them to your doctor’s attention.

It may take longer than usual to stop bleeding when taking ticlopidine hydrochloride tablets. Tell your doctor if you have any more bleeding or bruising than usual, and, if you have emergency surgery, be sure to let your doctor or dentist know that you are taking ticlopidine hydrochloride tablets. Also, tell your doctor well in advance of any planned surgery (including tooth extraction), because he or she may recommend that you stop taking ticlopidine hydrochloride tablets temporarily.

How Ticlopidine Hydrochloride Tablets Work:

Stroke Patients: A stroke occurs when a clot (or thrombus) forms in a blood vessel in the brain or forms in another part of the body and breaks off, then travels to the brain (an embolus). In both cases the blood supply to part of the brain is blocked and that part of the brain is damaged. Ticlopidine hydrochloride tablets work by making the blood less likely to clot, although not so much less that it causes you to become likely to bleed, unless you have a bleeding disorder or some injury (such as a bleeding ulcer of the stomach or intestine) that is especially likely to bleed.

Stent Patients: A heart attack or angina (chest pain) can occur when fatty deposits block the arteries that carry oxygen and nutrient-rich blood to your heart. To decrease the chance of fatty deposits building up over time, your doctor may recommend the placement of a coronary stent. Ticlopidine hydrochloride tablets may be given to you with aspirin to make blood clots less likely to form inside the stent so that the artery remains open.

Who Should Not Take Ticlopidine Hydrochloride Tablets? Contact your doctor immediately and do not take ticlopidine hydrochloride tablets if:

- you have an allergic reaction to ticlopidine hydrochloride tablets
- you have a blood disorder or a serious bleeding problem, such as a bleeding stomach ulcer
- you have previously been told you had TTP or aplastic anemia
- you have severe liver disease or other liver problems
- you are pregnant or you are planning to become pregnant
- you are breast-feeding

Manufactured In Israel By:

TEVA PHARMACEUTICAL IND. LTD.

Jerusalem, 91010, Israel

Manufactured For:

TEVA PHARMACEUTICALS USA

Sellersville, PA 18960

Rev. H 2/2012

TICLOPIDINE HYDROCHLORIDE TABLET, FILM COATED

TICLOPIDINE HYDROCHLORIDE Tablets USP 250 mg Label text

0093- -01 NDC 0154

TICLOPIDINE

HYDROCHLORIDE

Tablets USP

250 mg

PHARMACIST: PLEASE

DISPENSE WITH ATTACHED

PATIENT INFORMATION LEAFLET

Rx only

100 TABLETS

TEVA